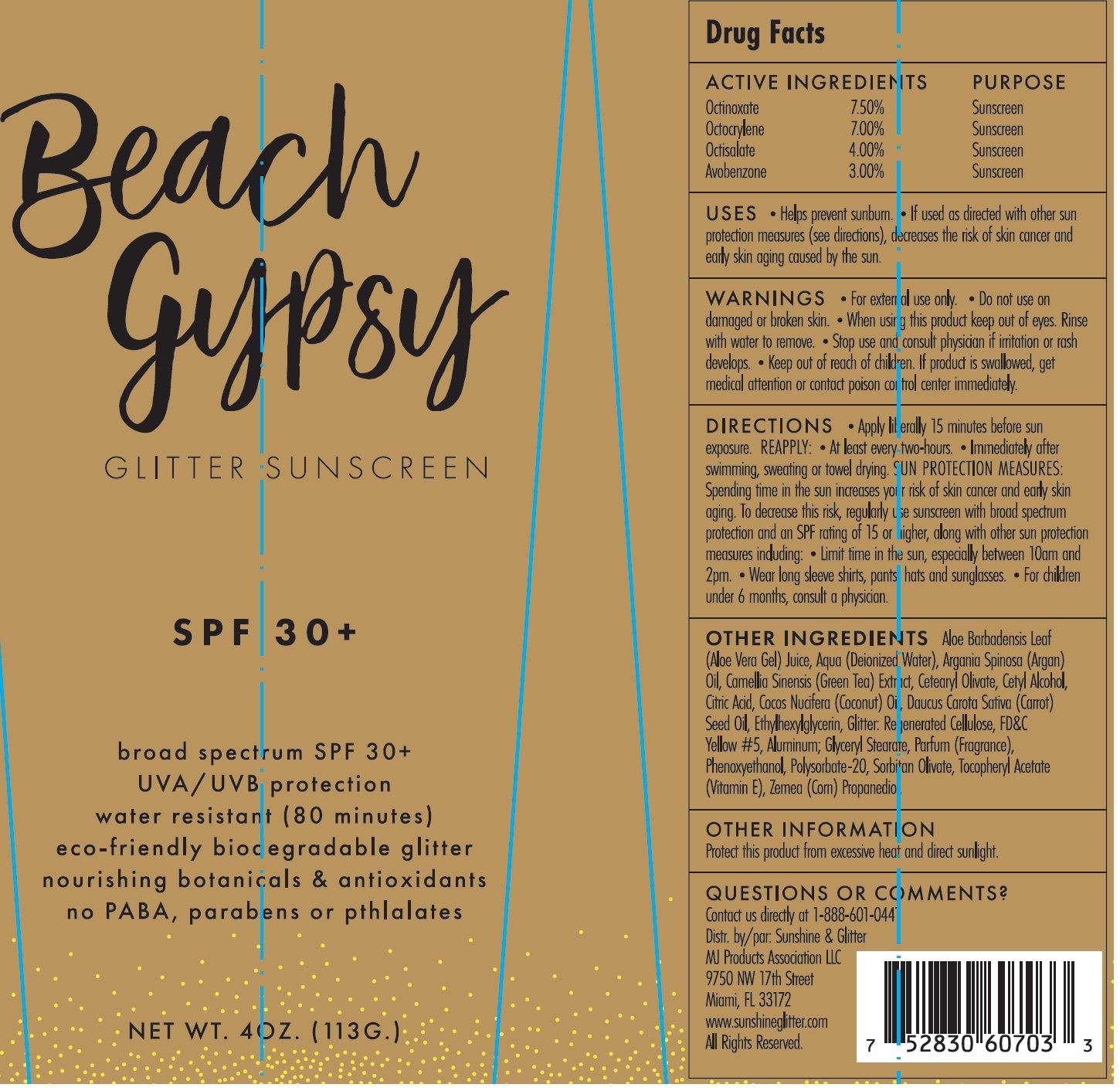 DRUG LABEL: Beach Gypsy SPF-30
NDC: 72085-146 | Form: CREAM
Manufacturer: MJ Products Association, LLC
Category: otc | Type: HUMAN OTC DRUG LABEL
Date: 20231115

ACTIVE INGREDIENTS: OCTINOXATE 75 mg/1 g; OCTOCRYLENE 70 mg/1 g; OCTISALATE 40 mg/1 g; AVOBENZONE 30 mg/1 g
INACTIVE INGREDIENTS: ALOE VERA LEAF; WATER; ARGAN OIL; GREEN TEA LEAF; CETEARYL OLIVATE; CETYL ALCOHOL; CITRIC ACID MONOHYDRATE; COCONUT OIL; CARROT SEED OIL; ETHYLHEXYLGLYCERIN; REGENERATED CELLULOSE; FD&C YELLOW NO. 5; ALUMINUM; GLYCERYL MONOSTEARATE; PHENOXYETHANOL; POLYSORBATE 20; SORBITAN OLIVATE

Beach Gypsy SPF-30

ACTIVE INGREDIENTS

Octinoxate 7.50%

Octocrylene 7.00%

Octisalate 4.00%

Avobenzone 3.00%

PURPOSE

Sunscreen

USES

- Helps prevent sunburn.
- If used as directed with other sun protection measures (see directions), decreases the risk of skin cancer and early skin aging caused by the sun.

WARNINGS

- For external use only.

Do not use

on damaged or broken skin

When using this product

keep out of eyes. Rinse with water to remove.

Stop use and consult physician

if irritation or rash develops.

Keep out of reach of children.

If product is swallowed, get medical attention or contact poison control center immediately.

DIRECTIONS

- Apply liberally 15 minutes before sun exposure. REAPPLY:
- Al least every two-hours.
- Immediately after swimming, sweating or towel drying. : Spending time in the sun increases your risk of skin cancer and early skin aging. To decreases this risk, regularly use sunscreen with broad spectrum protection and an SPF rating of 15 or higher, along with other sun protection measures including: SUN PROTECTION MEASURES
- Limit time in the sun, especially between 10am and 2pm.
- Wear long sleeve shirts, pants hats and sunglasses.
- For children under 6 months, consult a physician.

OTHER INGREDIENTS

Aloe Barbadensis Leaf (Aloe Vera Gel) Juice, Aqua (Deionized Water), Argania Spinosa (Argan) Oil, Camellia Sinensis (Green Tea) Extract, Cetearyl Olivate, Cetyl Alcohol, Citric Acid, Cocos Nucifera (Coconut) Oil, Daucus Carota Sativa (Carrot) Seed Oil, Ethylhexylglycerin, Glitter: Regenerated Cellulose, FD&C Yellow #5, Aluminum; Glyceryl Stearate, Parfum (Fragrance), Phenoxyethanol, Polysorbate-20, Sorbitan Olivate, Tocopheryl Acetate (Vitamin E), Zemea (Corn) Propanedio.

OTHER INFORMATION

Protect this product from excessive heat and direct sunlight.

QUESTIONS OR COMMENTS?

Contact us directly at 1-888-601-0441

Distr. by/par: Sunshine & Glitter

MJ Products Association LLC

9750 NW 17th Street

Miami, FL 33172

www.sunshineglitter.com

All Rights Reserved.